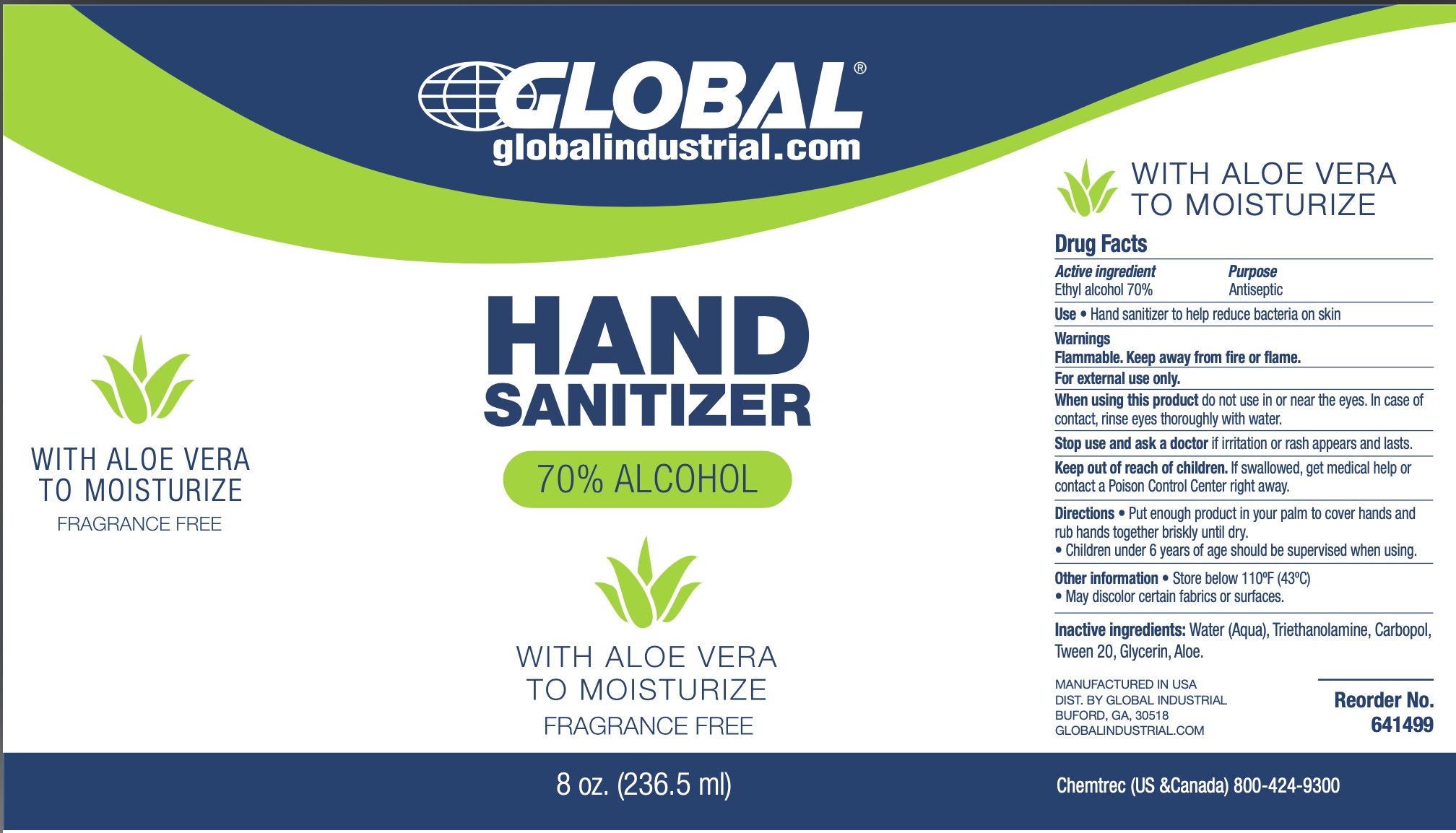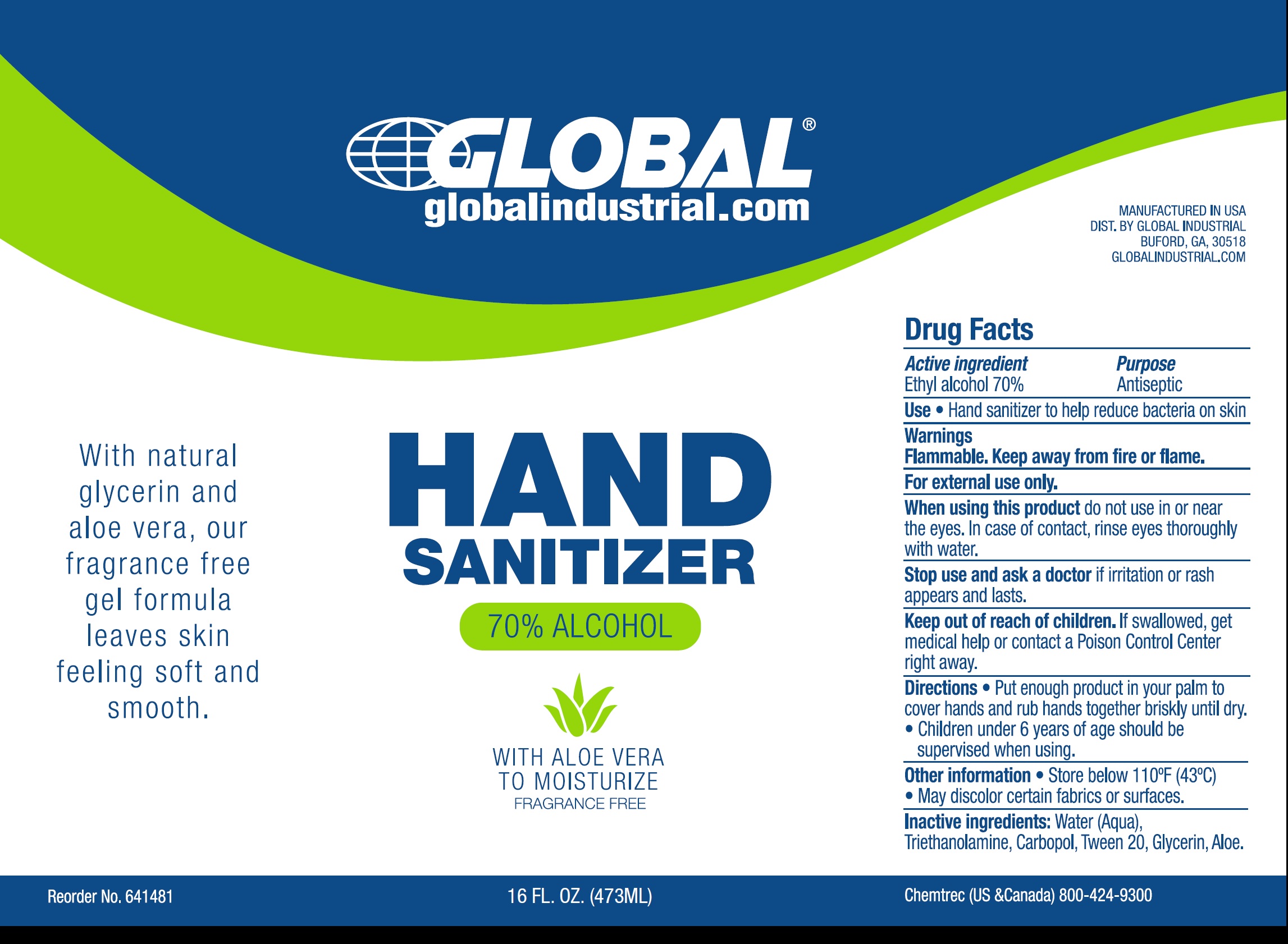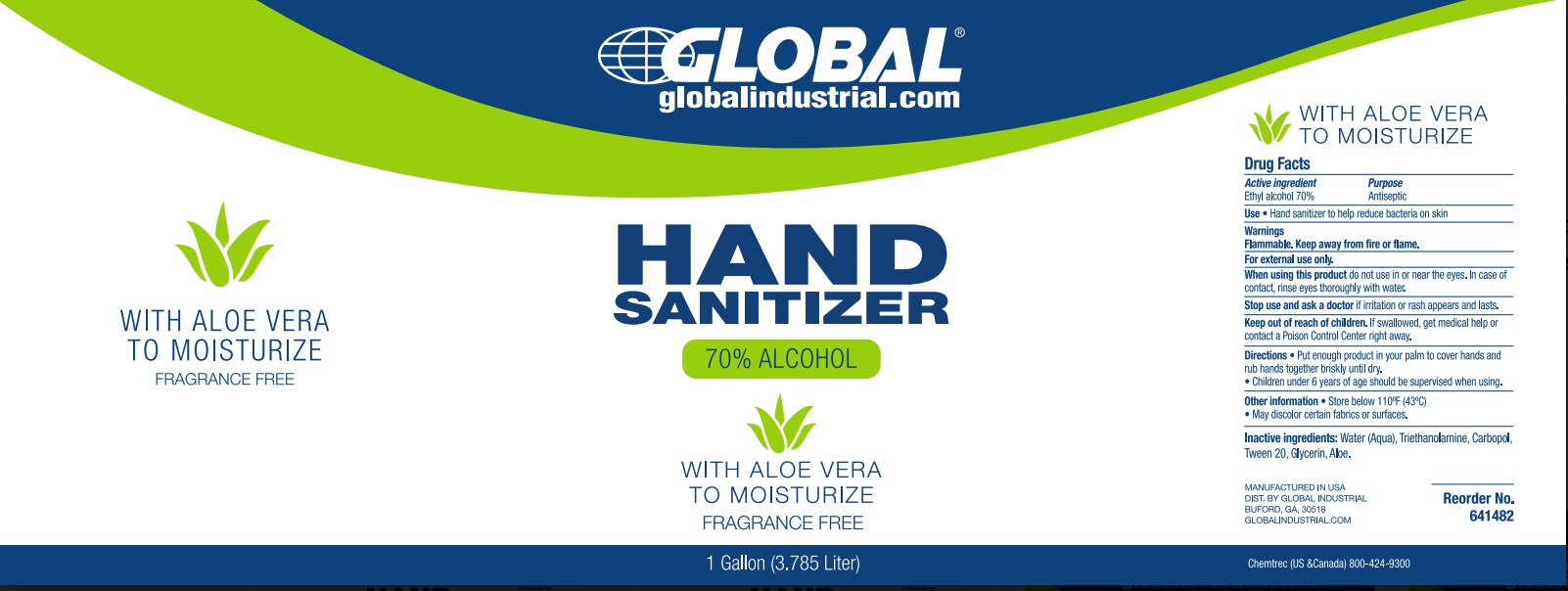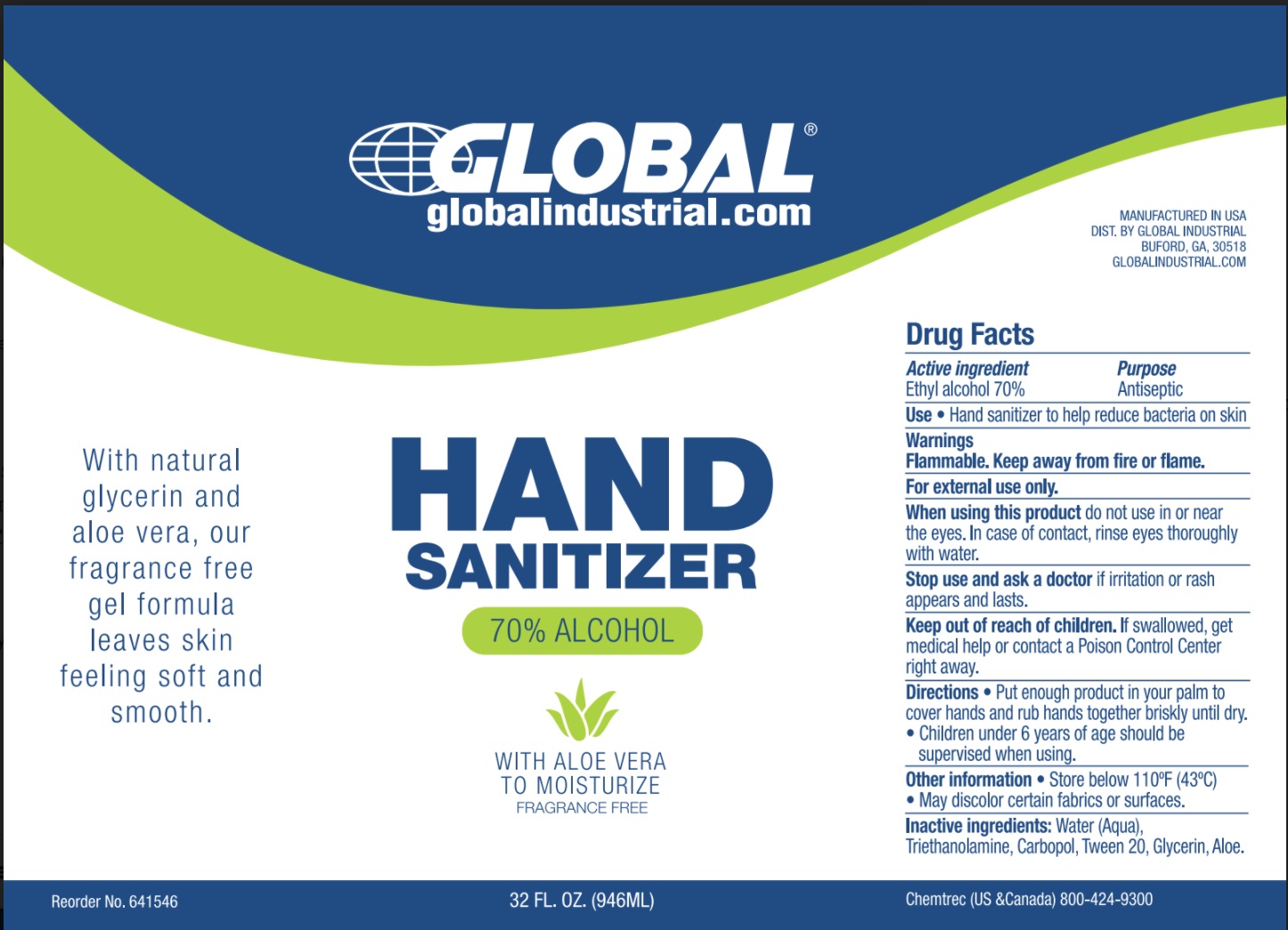 DRUG LABEL: Global Industrial Hand Sanitizer with Aloe
NDC: 78641-001 | Form: GEL
Manufacturer: Global Equipment Company Inc.
Category: otc | Type: HUMAN OTC DRUG LABEL
Date: 20240520

ACTIVE INGREDIENTS: ALCOHOL 0.7 mL/1 mL
INACTIVE INGREDIENTS: WATER; TROLAMINE; CARBOMER HOMOPOLYMER, UNSPECIFIED TYPE; POLYSORBATE 20; GLYCERIN; ALOE

Global Industrial Hand Sanitizer with Aloe

Active ingredient

Ethyl alcohol 70%

Purpose

Antiseptic

Use

- Hand sanitizer to help reduce bacteria on the skin

Warnings

Flammable. Keep away from fire or flame.

For external use only.

When using this product

do not use in or near the eyes. In case of contact, rinse eyes thoroughly with water

Stop use and ask a doctor

if irritation or rash appears and lasts.

Keep out of reach of children.

If swallowed, get medical help or contact a Poison Control Center right away.

Directions

- Put enough product in your palm to cover hands and rub hands together briskly until dry.
- Children under 6 years of age should be supervised when using.

Other information

- Store below 110°F (43°C)
- May discolor certain fabrics or surfaces.

Inactive ingredients:

Water (Aqua), Triethanolamine, Carbopol, Tween 20, Glycerin, Aloe.